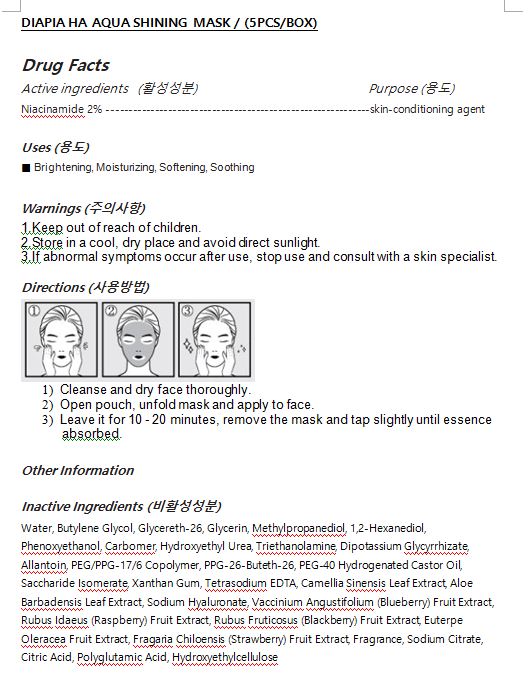 DRUG LABEL: DIAPIA HA AQUA SHINING MASK
NDC: 71857-0013 | Form: LIQUID
Manufacturer: BSG H & B Co., Ltd.
Category: otc | Type: HUMAN OTC DRUG LABEL
Date: 20201029

ACTIVE INGREDIENTS: NIACINAMIDE 2 g/100 mL
INACTIVE INGREDIENTS: WATER

Drug Facts

ACTIVE INGREDIENT

Niacinamide

INACTIVE INGREDIENT

Water, Butylene Glycol, Glycereth-26, Glycerin, Methylpropanediol, 1,2-Hexanediol, Phenoxyethanol, Carbomer, Hydroxyethyl Urea, Triethanolamine, Dipotassium Glycyrrhizate, Allantoin, PEG/PPG-17/6 Copolymer, PPG-26-Buteth-26, PEG-40 Hydrogenated Castor Oil, Saccharide Isomerate, Xanthan Gum, Tetrasodium EDTA, Camellia Sinensis Leaf Extract, Aloe Barbadensis Leaf Extract, Sodium Hyaluronate, Vaccinium Angustifolium (Blueberry) Fruit Extract,

Rubus Idaeus (Raspberry) Fruit Extract, Rubus Fruticosus (Blackberry) Fruit Extract, Euterpe Oleracea Fruit Extract, Fragaria Chiloensis (Strawberry) Fruit Extract, Fragrance, Sodium Citrate, Citric Acid, Polyglutamic Acid, Hydroxyethylcellulose

PURPOSE

Brightening, Moisturizing, Softening, Soothing

keep out of reach of the children

INDICATIONS AND USAGE

Cleanse and dry face thoroughly.

Open pouch, unfold mask and apply to face.

Leave it for 10 - 20 minutes, remove the mask and tap slightly until essence

absorbed.

WARNINGS

1.Keep out of reach of children.

2.Store in a cool, dry place and avoid direct sunlight.

3.If abnormal symptoms occur after use, stop use and consult with a skin specialist.

DOSAGE AND ADMINISTRATION

for external use only